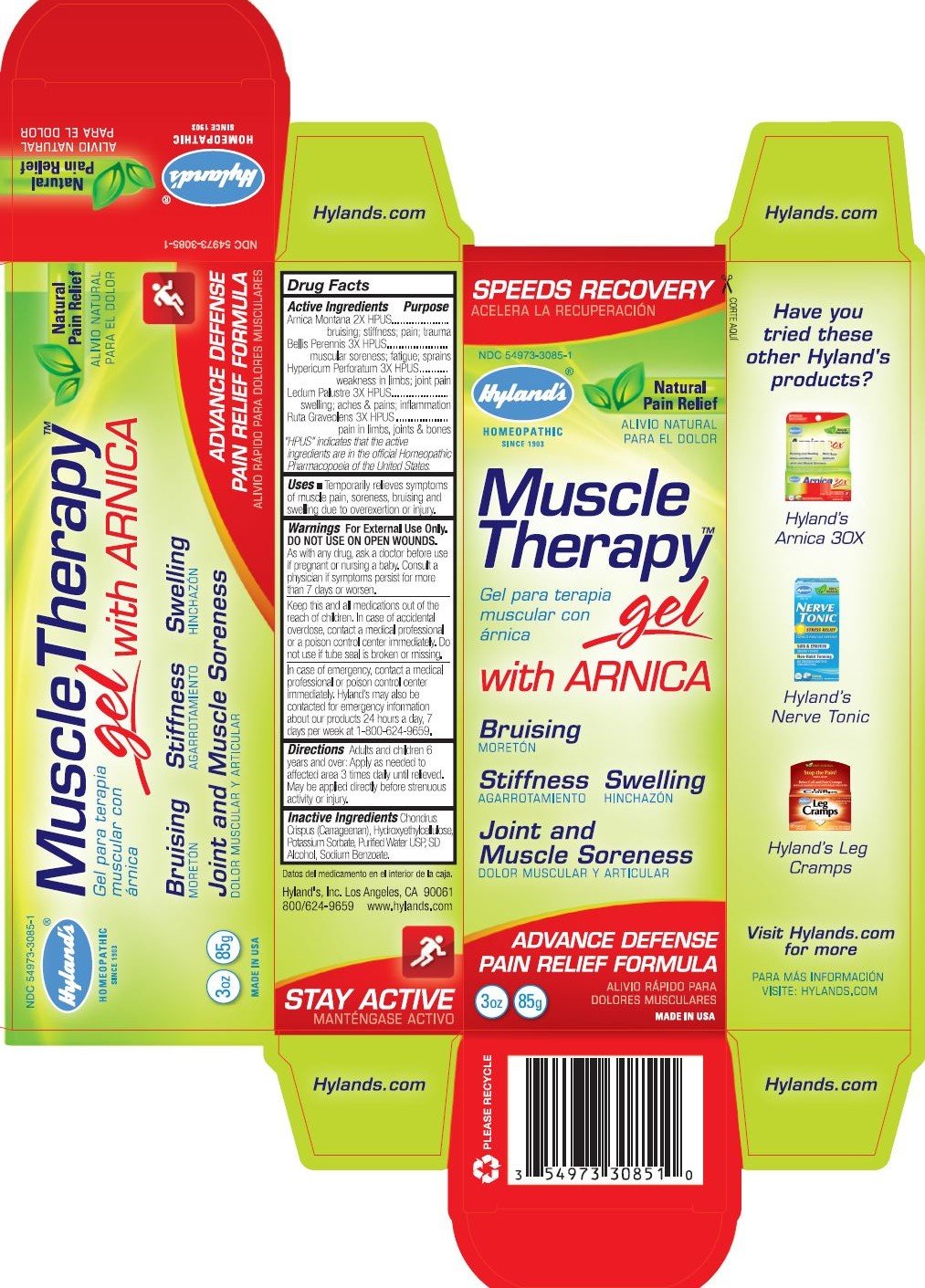 DRUG LABEL: MUSCLE THERAPY WITH ARNICA
NDC: 54973-3085 | Form: GEL
Manufacturer: Hyland's Inc.
Category: homeopathic | Type: HUMAN OTC DRUG LABEL
Date: 20221213

ACTIVE INGREDIENTS: ARNICA MONTANA 2 [hp_X]/1 g; BELLIS PERENNIS 3 [hp_X]/1 g; HYPERICUM PERFORATUM 3 [hp_X]/1 g; LEDUM PALUSTRE TWIG 3 [hp_X]/1 g; RUTA GRAVEOLENS FLOWERING TOP 3 [hp_X]/1 g
INACTIVE INGREDIENTS: CHONDRUS CRISPUS; HYDROXYETHYL CELLULOSE (5000 MPA.S AT 1%); POTASSIUM SORBATE; WATER; ALCOHOL; SODIUM BENZOATE

HYLAND'S MUSCLE THERAPY GEL WITH ARNICA

PURPOSE

Temporarily relieves the symptoms of muscle pain, soreness, bruising and swelling due to overexertion or injury.

Drug Facts

Active Ingredients | Purpose
Arnica Montana 2X HPUS | bruising; stiffness; pain; trauma
Bellis Perennis 3X HPUS | muscular soreness; fatigue; sprains
Hypericum Perforatum 3X HPUS | weakness in limbs; joint pain
Ledum Palustre 3X HPUS | swelling; aches & pains; inflammation
Ruta Graveolens 3X HPUS | pain in limbs, joints & bones

“HPUS” indicates that the active ingredients are in the official Homeopathic Pharmacopœia of the United States.

Uses

- Temporarily relieves the symptoms of muscle pain, soreness, bruising and swelling due to overexertion or injury.

Warnings

For External Use Only. DO NOT USE ON OPEN WOUNDS.

PREGNANCY OR BREAST FEEDING

As with any drug, ask a doctor before use if pregnant or nursing a baby. Consult a physician if symptoms persist for more than 7 days or worsen.

KEEP OUT OF REACH OF CHILDREN

Keep this and all medications out of the reach of children. In case of accidental overdose, contact a medical professional or a poison control center immediately. Do not use if tube seal is broken or missing.

In case of emergency, contact a medical professional or poison control center immediately. Hyland's may also be contacted for emergency information about our products 24 hours a day, 7 days per week at 1-800-624-9659.

Directions

Adults and children 6 years and over: Apply as needed to affected area 3 times daily until relieved. May be applied directly before strenuos activity or injury.

Inactive Ingredients

Chondrus Crispus (Carrageenan), Hydroxyethylcellulose,Potassium Sorbate,Purified Water USP,SD Alcohol,Sodium Benzoate.

PRINCIPAL DISPLAY PANEL - 85g Tube Carton

SPEEDS RECOVERY

NDC 54973-3085-1

Hyland's®

HOMEOPATHIC
SINCE 1903

Natural
Pain Relief

Muscle
Therapy™
gel
with ARNICA

Bruising
Stiffness Swelling
Joint and
Muscle Soreness

ADVANCE DEFENSE
PAIN RELIEF FORMULA

3oz 85g

MADE IN USA